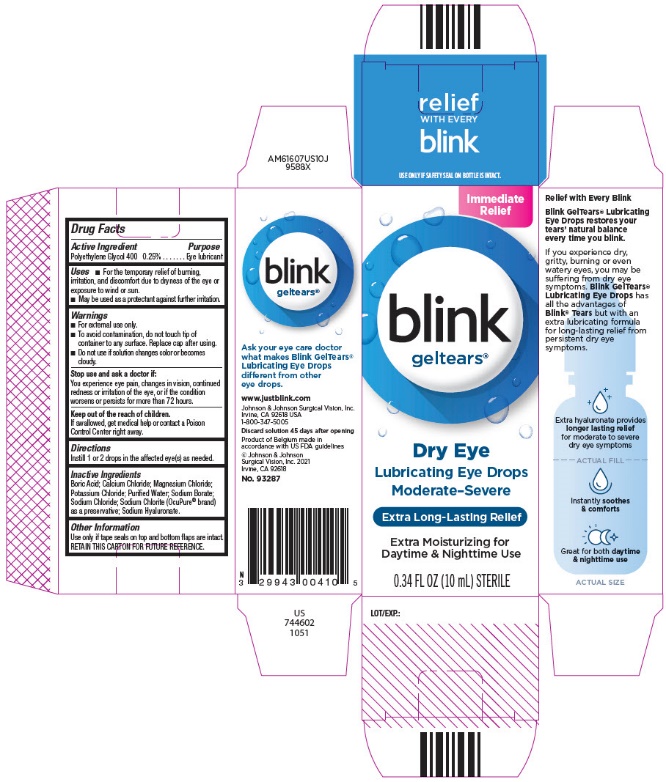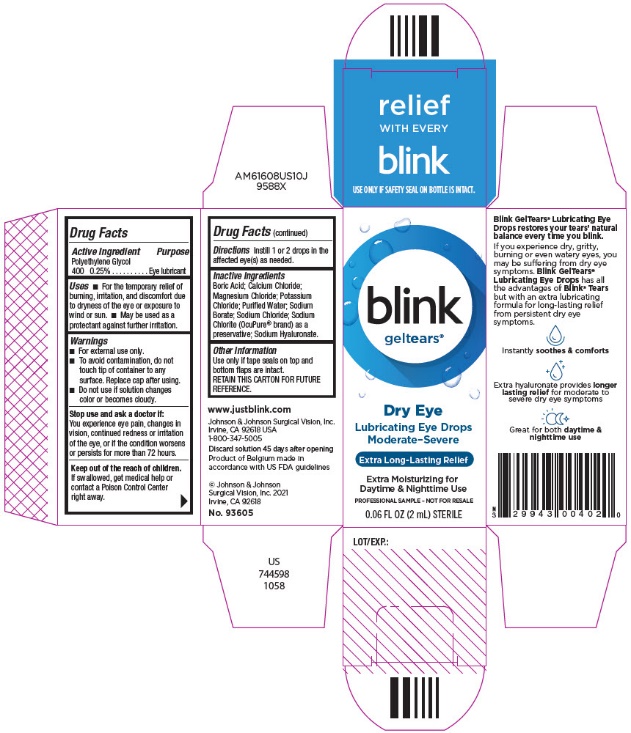 DRUG LABEL: blink gel tears
NDC: 29943-004 | Form: SOLUTION/ DROPS
Manufacturer: Bausch & Lomb Incorporated
Category: otc | Type: HUMAN OTC DRUG LABEL
Date: 20240920

ACTIVE INGREDIENTS: POLYETHYLENE GLYCOL 400 2.5 mg/1 mL
INACTIVE INGREDIENTS: BORIC ACID; CALCIUM CHLORIDE; MAGNESIUM CHLORIDE; POTASSIUM CHLORIDE; WATER; SODIUM BORATE; SODIUM CHLORIDE; SODIUM CHLORITE; HYALURONATE SODIUM

blink gel tears®

Drug Facts

OTC - ACTIVE INGREDIENT SECTION

Polyethylene Glycol 400 0.25%

Purpose

Eye lubricant

Uses

- For the temporary relief of burning, irritation and discomfort due to dryness of the eye or exposure to wind or sun.
- May be used as a protectant against further irritation.

WARNINGS

- For external use only.
- To avoid contamination, do not touch tip of container to any surface. Replace cap after using.
- Do not use if solution changes color or becomes cloudy.

Stop use and ask doctor if:

You experience eye pain, changes in vision, continued redness or irritation of the eye, or if the condition worsens or persists for more than 72 hours.

OTC - KEEP OUT OF REACH OF CHILDREN SECTION

Keep out of the reach of children.
If swallowed, get medical help of contact a Poison Control Center right away.

Directions

Instill 1 or 2 drops in the affected eye(s) as needed.

Other Information

Use only if tape seals on top and bottom flaps are intact.

RETAIN THIS CARTON FOR FUTURE REFERENCE.

INACTIVE INGREDIENT SECTION

Boric acid, calcium chloride, magnesium chloride, potassium chloride, purified water, sodium borate, sodium chloride, sodium chlorite (OcuPure®Brand) as a preservative; Sodium Hyaluronate.

OTC - QUESTIONS SECTION

In the U.S. call 1-800-347-5005

www.yourhealthyeyes.com

PRINCIPAL DISPLAY PANEL - 10 mL Bottle Carton

Immediate
Relief

blink
geltears®

Dry Eye

Lubricating Eye Drops

Moderate–Severe

Extra Long-Lasting Relief

Extra Moisturizing for
Daytime & Nighttime Use

0.34 FL OZ (10 mL) STERILE

PRINCIPAL DISPLAY PANEL - 2 mL Bottle Carton

blink
geltears®

Dry Eye

Lubricating Eye Drops

Moderate-Severe

Extra Long-Lasting Relief

Extra Moisturizing for
Daytime & Nighttime Use

PROFESSIONAL SAMPLE - NOT FOR RESALE

0.06 FL OZ (2 mL) STERILE